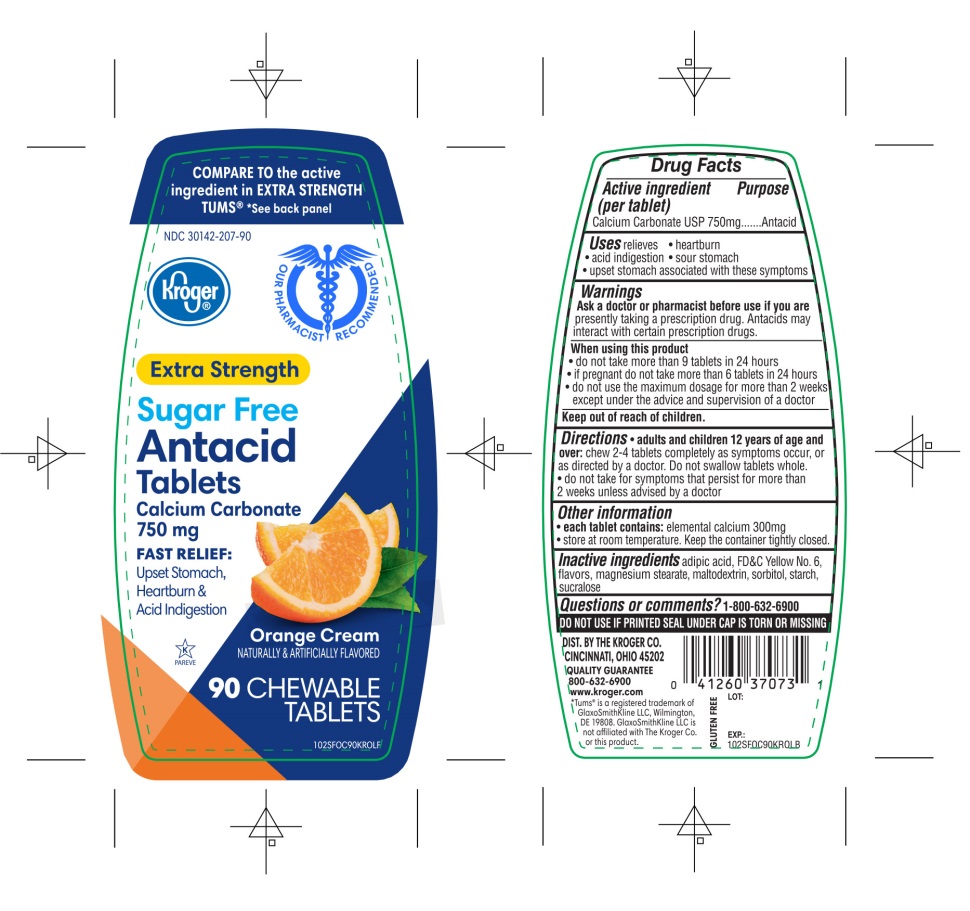 DRUG LABEL: Kroger Extra Strength

NDC: 30142-207 | Form: TABLET, CHEWABLE
Manufacturer: KROGER COMPANY
Category: otc | Type: HUMAN OTC DRUG LABEL
Date: 20250801

ACTIVE INGREDIENTS: CALCIUM CARBONATE 750 mg/1 1
INACTIVE INGREDIENTS: ADIPIC ACID; FD&C YELLOW NO. 6; MAGNESIUM STEARATE; MALTODEXTRIN; SORBITOL; STARCH, CORN; SUCRALOSE

Extra Strength Antacid Tablets Calcium Carbonate 750 mg

Active ingredient (per tablet)

Calcium Carbonate USP 750 mg

Purpose

Antacid

Uses

relieves

- heartburn
- acid indigestion
- sour stomach
- upset stomach associated with these symptoms

Warnings

Ask a doctor or pharmacist before use if you arepresently taking a prescription drug. Antacids may interact with certain prescription drugs.

When using this product

- do not take more than 9 tablets in 24 hours
- if pregnant do not take more than 6 tablets in 24 hours
- do not use the maximum dosage for more than 2 weeks except under the advice and supervision of a doctor.

Directions

- adults and children 12 years of age and over:chew 2-4 tablets completely as symptoms occur, or as directed by a doctor. Do not swallow tablets whole.
- do not take for symptoms that persist for more than 2 weeks except under the advice and supervision of a doctor.

Other Information

- each tablet contains:elemental calcium 300mg
- Store at room temperature. Keep the container tightly closed

Safety sealed: DO NOT USE IF PRINTED SEAL UNDER CAP IS TORN OR MISSING

Questions or comments?

1-800-632-6900

Inactive ingredients

adipic acid, FD&C Yellow No. 6, flavors, magnesium stearate, maltodextrin, sorbitol, starch, sucralose.

Questions or comments?

1-800-632-6900

Package/Label Principal Display Panel

NDC 30142-207-90

Kroger®

FOR OUR FAMILY TO YOURS

COMPARE TO the active ingredient in EXTRA STRENGTH TUMS®

**See back panel

Sugar Free

EXTRA STRENGTH

Antacid Tablets

Calcium Carbonate USP 750 mg

Orange Cream Flavor

NATURALLY & ARTIFICIALLY FLAVORED

- FAST RELIEF OF UPSET STOMACH, HEARTBURN AND ACID INDEGESTION
- GLUTEN FREE

90 CHEWABLE TABLETS

K PARVE

Distributed by:

THE KROGER CO. CINCINNATI, OHIO 45202

QUALITY GUARANTEE

1800-632-6900 www.kroger.com

**TUMS®is registered trademark of GlaxoSmithKline LLC, Wilmington, DE 19808. GlaxoSmithKline LLC is not affiliated with The Kroger Co. or this product.